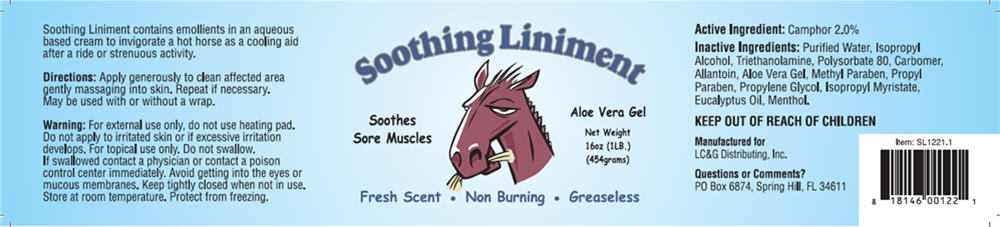 DRUG LABEL: Soothing Liniment
NDC: 24465-833 | Form: CREAM
Manufacturer: LC&G Distributing Inc.
Category: animal | Type: OTC ANIMAL DRUG LABEL
Date: 20120919

ACTIVE INGREDIENTS: CAMPHOR (SYNTHETIC) 2 g/100 g
INACTIVE INGREDIENTS: Water; Isopropyl Alcohol; Trolamine; Polysorbate 80; Carbomer Homopolymer TYPE C (Allyl Pentaerythritol Crosslinked); Allantoin; Aloe Vera Leaf; Methylparaben Sodium; Propylparaben Sodium; Propylene Glycol; Isopropyl Myristate; Eucalyptus Oil; Menthol

Soothing Liniment
Aloe Vera Gel

Active Ingredient

Camphor 2.0%

Inactive Ingredients

Purified Water, Isopropyl Alcohol, Triethanolamine, Polysorbate 80, Carbomer, Allantoin, Aloe Vera Gel, Methyl Paraben, Propyl Paraben, Propylene Glycol, Isopropyl Myristate, Eucalyptus Oil, Menthol.

KEEP OUT OF REACH OF CHILDREN

Directions

Apply generously to clean affected area gently massaging into skin. Repeat if necessary. May be used with or without a wrap.

Warning

DO NOT USE

For external use only, do not use heating pad. Do not apply to irritated skin or if excessive irritation develops.

WHEN USING

For topical use only. Do not swallow. If swallowed contact a physician or contact a poison control center immediately. Avoid getting into eyes or mucous membranes.

STORAGE AND HANDLING

Keep tightly closed when not in use. Store at room temperature. Protect from freezing.

Questions or Comments?

PO Box 6874, Spring Hill, FL 34611

Manufactured for
LC&G Distributing, Inc.

PRINCIPAL DISPLAY PANEL - 454 grams Bottle Label

Soothing Liniment

Soothes
Sore Muscles

Aloe Vera Gel

Net Weight
16oz (1LB.)
(454grams)

Fresh Scent ∙ Non Burning ∙ Greaseless